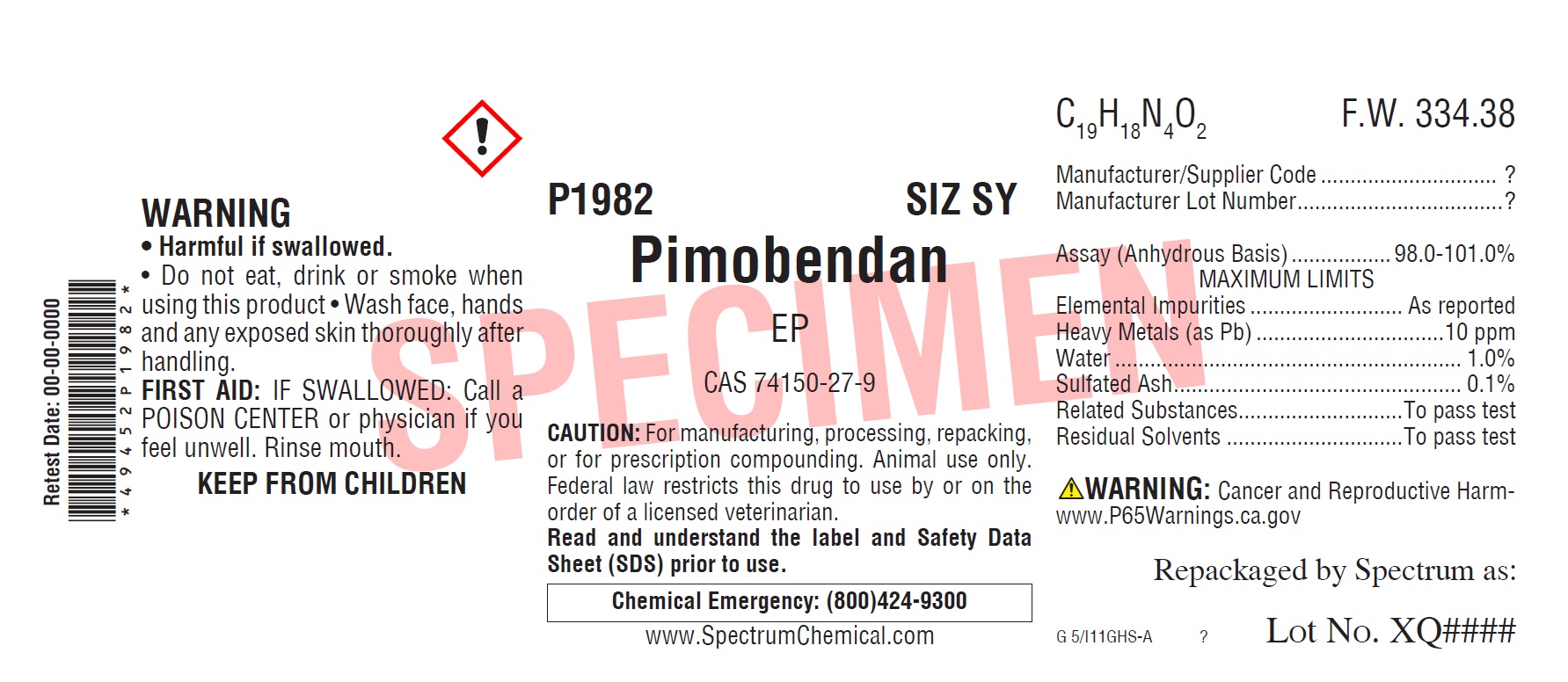 DRUG LABEL: Pimobendan
NDC: 49452-5072 | Form: POWDER
Manufacturer: Spectrum Laboratory Products, Inc.
Category: other | Type: BULK INGREDIENT
Date: 20210126

ACTIVE INGREDIENTS: PIMOBENDAN 1 g/1 g

Pimobendan